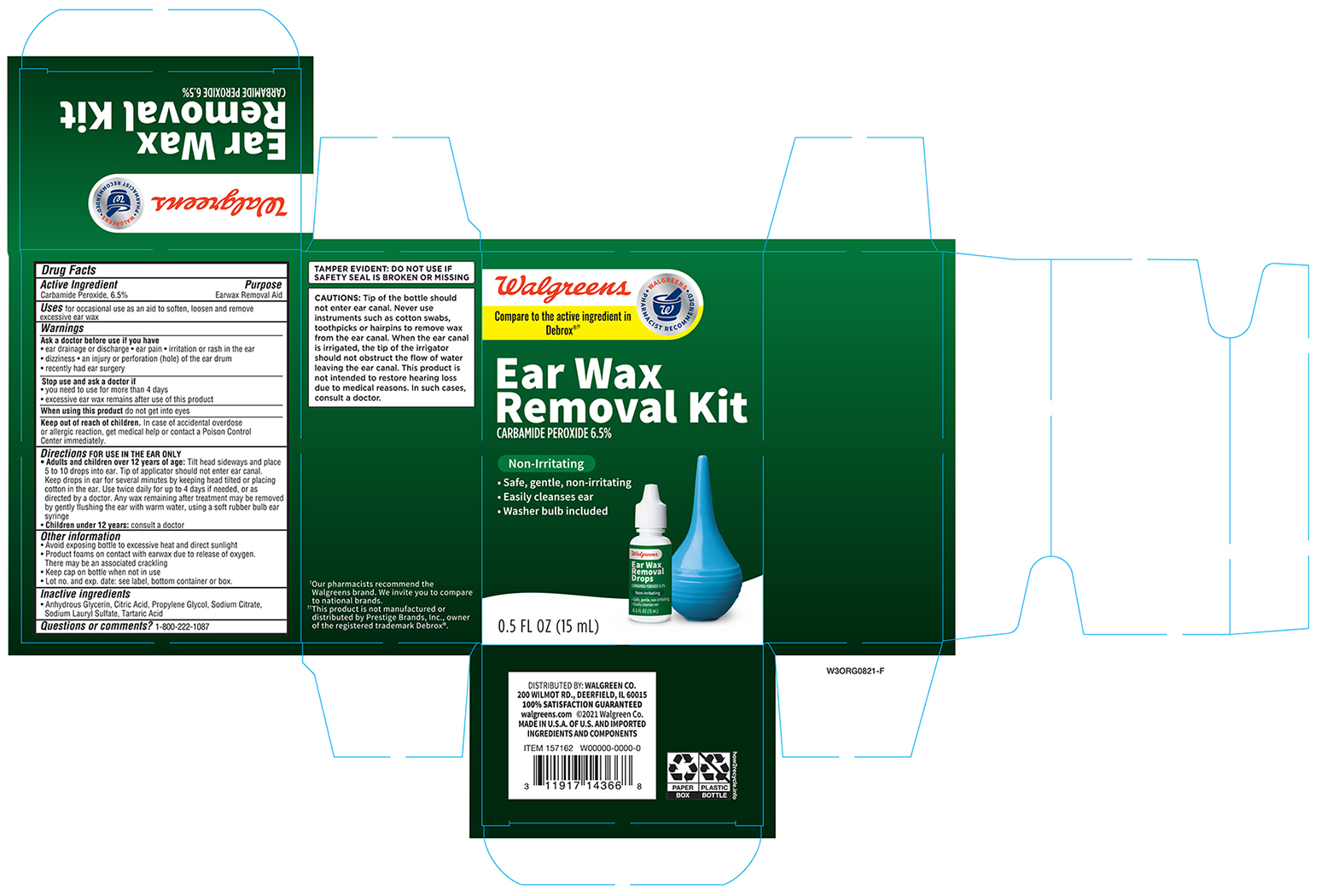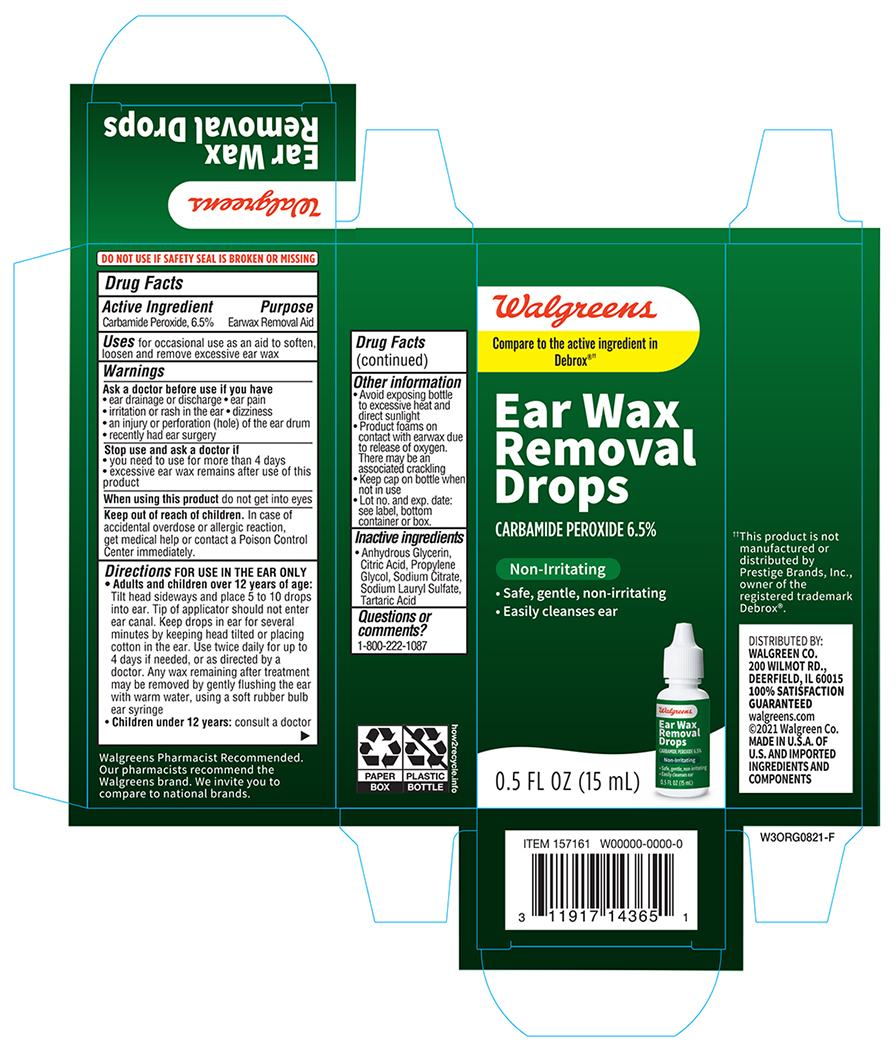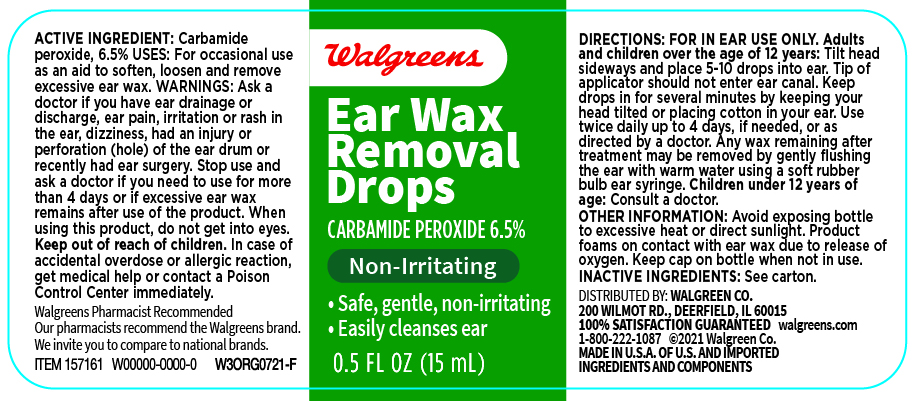 DRUG LABEL: Walgreens Ear Wax Remover
NDC: 0363-2068 | Form: LIQUID
Manufacturer: Walgreens Company
Category: otc | Type: HUMAN OTC DRUG LABEL
Date: 20241120

ACTIVE INGREDIENTS: CARBAMIDE PEROXIDE 0.065 mg/1 mL
INACTIVE INGREDIENTS: GLYCERIN; ANHYDROUS CITRIC ACID; PROPYLENE GLYCOL; SODIUM CITRATE; SODIUM LAURYL SULFATE; TARTARIC ACID

Walgreens Ear Wax Remover

Active ingredient

Carbamide Peroxide 6.5%

Purpose

Ear Wax Removal Aid

Uses

For occasional use as an aid to soften, loosen and remove excessive ear wax.

Warnings

Ask a Doctor before use if you have

- eardrainage, discharge, ear pain,irritation
- rash in the ear,or are dizzy
- injury or perforation (hole) of the ear drum
- Recently had ear surgery

Stop Use and ask a Doctor if

- you need to use for more than 4 days
- execessive ear wax remain after use of this product

When using this product

do not use for more than four days
avoid contact with the eyes. If accidental contact with the eyes occurs, flush eyes with water and consult a doctor
if excessive earwax remains after the use of this product, consult a doctor

Keep out of the reach of children

If swallowed, get medical help or contact a Poison Control Center right away.

Directions FOR USE IN THE EAR ONLY

Adults and children over 12 years of age:

- Tilt head sideways and place 5 to 10 drops into ear.
- Tip of applicator should not enter ear canal.
- Keep drops in ear for several minutes by keeping head tilted or placing cotton in the ear.
- Use twice daily for up to 4 days if needed, or as directed by a doctor.
- Any earwax remaining after treatment may be removed by gently flushing the ear with warm water, using a soft rubber bulb ear syringe.
- When the ear canal is irrigated, the tip of the ear syringe should not obstruct the flow of water leaving the ear canal.

Children under 12 years: consult a doctor.

Inactive Ingredients

Citric Acid, Glycerin, Propylene Glycol, Sodium Citrate, Sodium Lauryl Sulfate, Tartaric Acid

Other information

Protect from heat and direct sunlight
product foams on contact with ear wax due ot releae of oxygen, there may be associated cracking
Keep cap on bottle when not in use.
Lot No. and EXP date: see label, bottom container or box.

Principal Display Panel Bottle Label 0.5 FL OZ

Walgreens Ear Wax Remover NDC 0363-2068-15

Ear Wax Removal drops

Carbamide Peroxide 6.5%

0.5 FL OZ (15ml)

Principal Display Panel Carton Label 0.5 FL OZ

Walgreens Ear Wax Remover NDC 0363-2068-15

Ear Wax Removal drops

Carbamide Peroxide 6.5%

0.5 FL OZ (15ml)

Principal Display Panel Kit Label 0.5 FL OZ

Walgreens Ear Wax Remover Kit NDC 0363-2068-25

Ear Wax Removal drops

Carbamide Peroxide 6.5%

0.5 FL OZ (15ml)